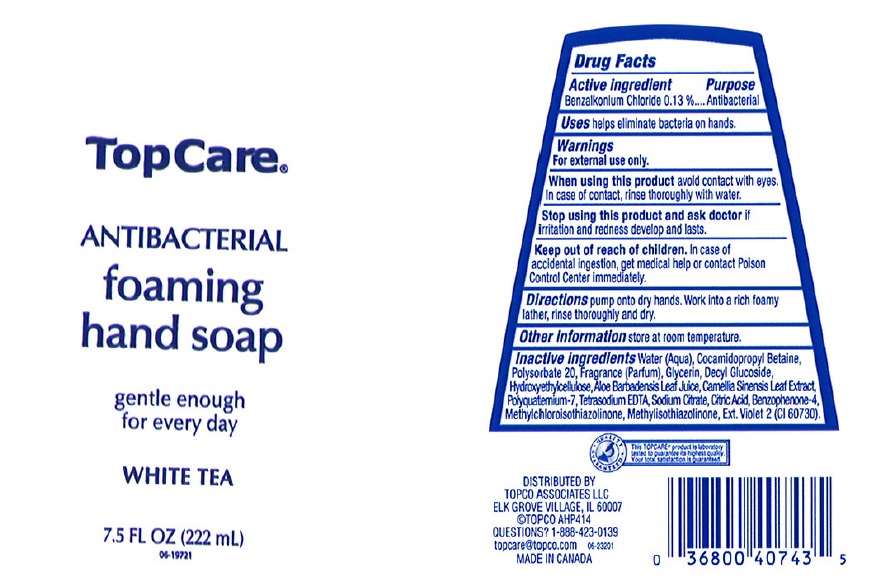 DRUG LABEL: Topcare
NDC: 36800-273 | Form: LIQUID
Manufacturer: Topco Associates LLC
Category: otc | Type: HUMAN OTC DRUG LABEL
Date: 20170407

ACTIVE INGREDIENTS: BENZALKONIUM CHLORIDE 1.3 mg/1 mL
INACTIVE INGREDIENTS: WATER; COCAMIDOPROPYL BETAINE; POLYSORBATE 20; GLYCERIN; DECYL GLUCOSIDE; HYDROXYETHYL CELLULOSE (5000 CPS AT 1%); ALOE VERA LEAF; GREEN TEA LEAF; EDETATE SODIUM; SODIUM CITRATE; CITRIC ACID MONOHYDRATE; SULISOBENZONE; METHYLCHLOROISOTHIAZOLINONE; METHYLISOTHIAZOLINONE; EXT. D&C VIOLET NO. 2

Drug Facts

Active ingredient

Benzalkonium Chloride 0.13%

Purpose

Antibacterial

Uses

Helps eliminate bacteria on hands

Warnnigs

For external use only.

When using this product

Avoid contact with eyes. In case of contact, rinse thoroughly with water.

Stop using this product and ask doctor if

irritation and redness develop and last.

Keep out of reach of children.

In case of accidental ingestion, get medical help or contact a Poison Control Center immediately.

Directions

Pump onto dry hands. Work into a rich foamy lather, rinse thoroughly and dry.

Other information

Store at room temperature.

Inactive ingredients

Water (Aqua), Cocamidopropyl Betaine, Polysorbate 20, Fragrance (Parfum), Glycerin, Decyl Glucoside, Hydroxyethylcellulose, Aloe Barbadensis Leaf Juice, Camellia Sinensis Leaf Extract, Polyquaternium-7, Tetrasodium EDTA, Sodium Citrate, Citric Acid, Benzophenone-4, Methylchloroisothiazolinone, Methylisothiazolinone, Ext. Violet 2 (CI 60730).